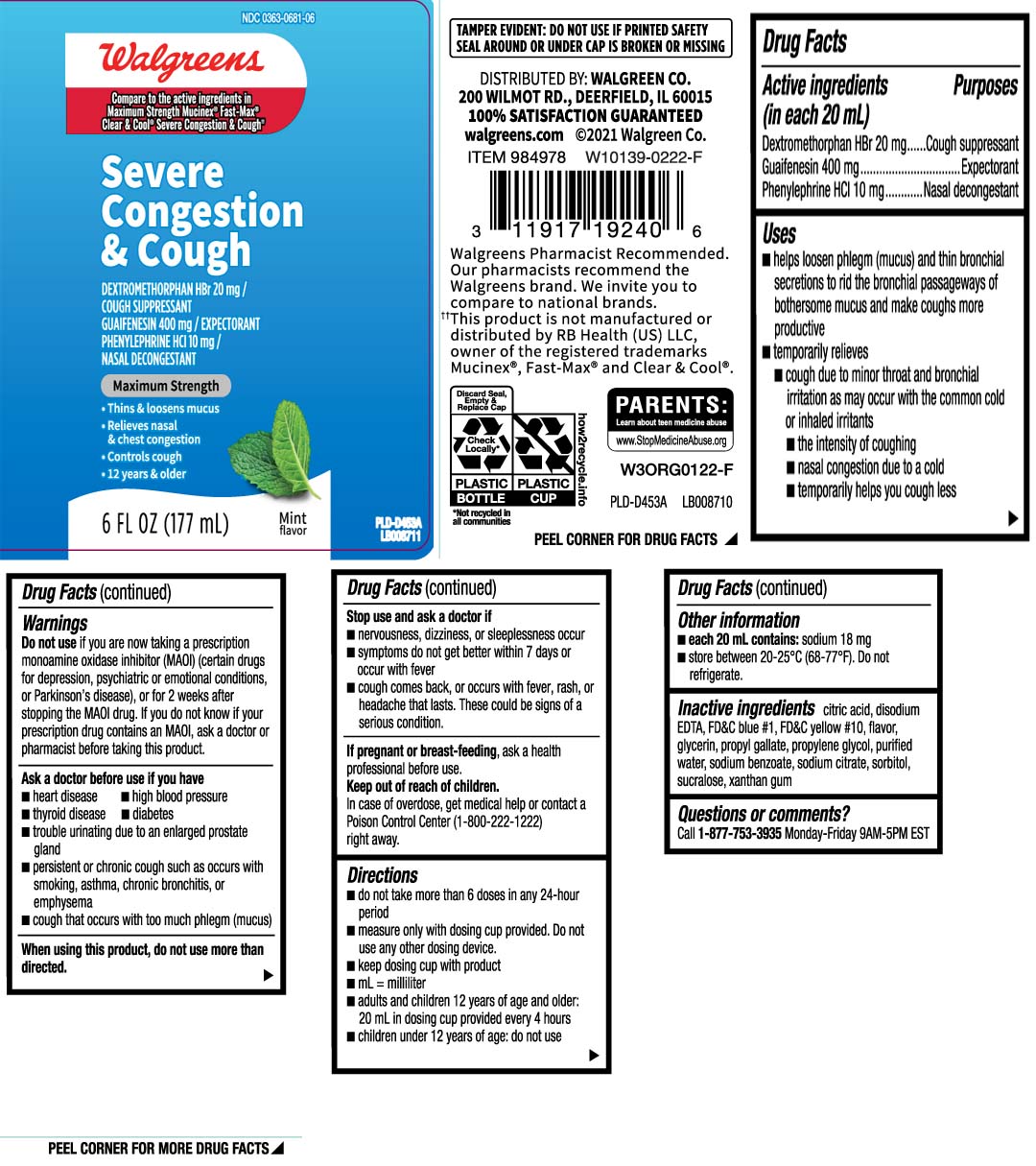 DRUG LABEL: Mucus Relief Severe Congestion and Cough
NDC: 0363-0681 | Form: LIQUID
Manufacturer: Walgreens
Category: otc | Type: HUMAN OTC DRUG LABEL
Date: 20240717

ACTIVE INGREDIENTS: DEXTROMETHORPHAN HYDROBROMIDE 20 mg/20 mL; GUAIFENESIN 400 mg/20 mL; PHENYLEPHRINE HYDROCHLORIDE 10 mg/20 mL
INACTIVE INGREDIENTS: ANHYDROUS CITRIC ACID; EDETATE DISODIUM; FD&C BLUE NO. 1; GLYCERIN; PROPYL GALLATE; PROPYLENE GLYCOL; WATER; SODIUM BENZOATE; TRISODIUM CITRATE DIHYDRATE; SORBITOL; SUCRALOSE; XANTHAN GUM; D&C YELLOW NO. 10

Drug Facts

Active ingredients (in each 20 mL)

Dextromethorphan HBr 20 mg

Guaifenesin 400 mg

Phenylephrine HCL 10 mg

Purpose

Cough suppressant

Expectorant

Nasal decongestant

Uses

- helps loosen phlegm (mucus) and thin bronchial secretions to rid the bronchial passageways of bothersome mucus and make coughs more productive
- temporarily relieves:
  - cough due to minor throat and bronchial irritation as may occur with the common cold or inhaled irritants
  - the intensity of coughing
  - temporarily help you cough less
  - nasal congestion due to a cold

Warnings

Do not use

if you are now taking a prescription monoamine oxidase inhibitor (MAOI) (certain drugs for depression, psychiatric or emotional conditions, or Parkinson's disease), or for 2 weeks after stopping the MAOI drug. If you do not know if your prescription drug contains an MAOI, ask a doctor or pharmacist before taking this product.

Ask a doctor before use if you have

- heart disease
- high blood pressure
- thyroid disease
- diabetes
- trouble urinating due to an enlarged prostate gland
- persistent or chronic cough such as occurs with smoking, asthma, chronic bronchitis or emphysema
- cough that occurs with too much phlegm (mucus)

When using this product,

do not use more than directed

Stop use and ask a doctor if

- nervousness, dizziness or sleeplessness occur
- symptoms do not get better within 7 days or occur with fever
- cough comes back, or occurs with fever, rash or headache that lasts. These could be signs of a serious condition.

If pregnant or breast-feeding,

ask a health professional before use.

Keep out of reach of children.

In case of overdose, get medical help or contact a Poison Control Center (1-800-222-1222) right away.

Directions

- do not take more than 6 doses in a 24-hour period
- measure only with dosing cup provided. Do not use any other dosing device
- keep dosing cup with device
- mL = milliliter
- adults and children 12 years of age and older: 20 mL in dosing cup provided every 4 hours
- children under 12 years of age: do not use

Other information

- each 20 mL contains: sodium 18 mg
- store between 20-25ºC (68-77ºF). Do not refrigerate

Inactive ingredients

citric acid, disodium EDTA , FD&C blue #1, FD&C yellow #10, flavor, glycerin, propyl gallate, propylene glycol, purified water, sodium benzoate, sorbitol, sucralose, sodium citrate, xanthan gum

Questions or comments?

Call 1-877-753-3935 Monday-Friday 9AM-5PM EST

Principal Display Panel

Compare to the active ingredient in Maximum Strength Mucinex® Fast-Max® Clear & Cool® Severe Congestion & Cough††

Severe Congestion & Cough

DEXTROMETHORPHAN HBr 20 mg / COUGH SUPPRESSANT

GUAIFENESIN 400 mg / EXPECTORANT

PHENYLEPHRINE HCL 10 mg NASAL DECONGESTANT

MAXIMUM STRENGTH

- Thins & loosens mucus
- Relieves nasal & chest congestion
- Controls cough
- 12 years & older

MINT FLAVOR

FL OZ (mL)

††This product is not manufactured or distributed by RB Health (US) LLC, owner of the registered trademarks Mucinex® Fast-Max® and Clear & Cool®

TAMPER EVIDENT: DO NOT USE IF PRINTED SAFETY SEAL AROUND OR UNDER CAP IS BROKEN OR MISSING.

DISTRIBUTED BY: WALGREEN CO.

200 WILMOT RD., DEERFIELD, IL 60015

walgreens.com

Package Label

WALGREENS Mucus Relief Severe Congestion & Cough Mint Flavor